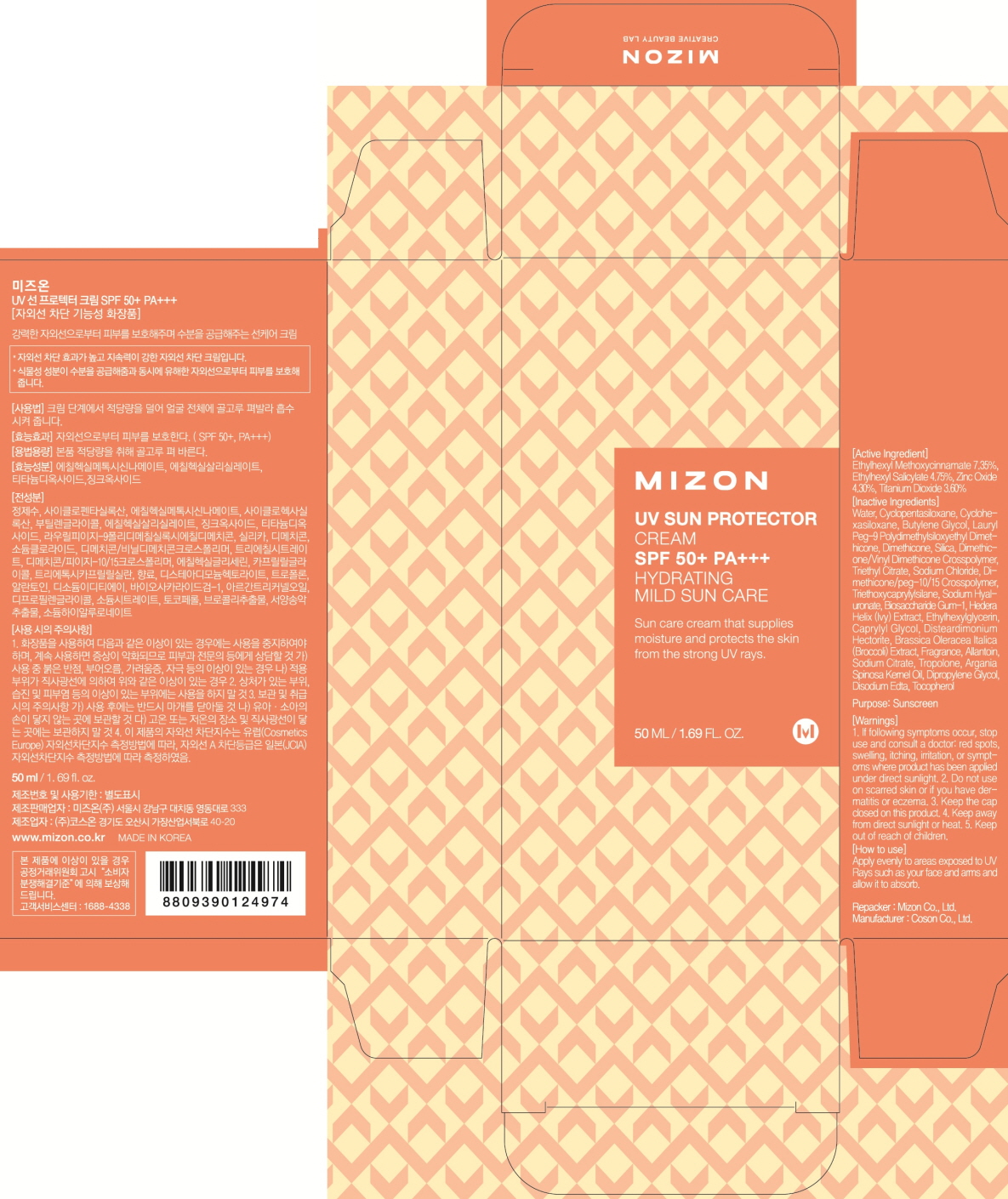 DRUG LABEL: MIZON UV SUN PROTECTOR
NDC: 57718-070 | Form: CREAM
Manufacturer: MIZON CO., LTD.
Category: otc | Type: HUMAN OTC DRUG LABEL
Date: 20160108

ACTIVE INGREDIENTS: Octinoxate 3.67 g/50 mL; Octisalate 2.37 g/50 mL; Zinc Oxide 2.15 g/50 mL; Titanium Dioxide 1.80 g/50 mL
INACTIVE INGREDIENTS: Water; Butylene Glycol

ACTIVE INGREDIENT

Active Ingredient: Ethylhexyl Methoxycinnamate 7.35%, Ethylhexyl Salicylate 4.75%, Zinc Oxide 4.30%, Titanium Dioxide 3.60%

INACTIVE INGREDIENT

Inactive Ingredients: Water, Cyclopentasiloxane, Cyclohexasiloxane, Butylene Glycol, Lauryl Peg-9 Polydimethylsiloxyethyl Dimethicone, Dimethicone, Silica, Dimethicone/Vinyl Dimethicone Crosspolymer, Triethyl Citrate, Sodium Chloride, DIMETHICONE/PEG-10/15 CROSSPOLYMER, Triethoxycaprylylsilane, Sodium Hyaluronate, Biosaccharide Gum-1, Hedera Helix(Ivy) Extract, Ethylhexylglycerin, Caprylyl Glycol, Disteardimonium Hectorite, Brassica Oleracea Italica(Broccoli) Extract, Fragrance, Allantoin, Sodium Citrate, Tropolone, Argania Spinosa Kernel Oil, Dipropylene Glycol, Disodium Edta, Tocopherol

PURPOSE

Purpose: Sunscreen

WARNINGS

Warnings: 1. If following symptoms occur, stop use and consult a doctor: red spots, swelling, itching, irritation, or symptoms where product has been applied under direct sunlight. 2. Do not use on scarred skin or if you have dermatitis or eczema. 3. Keep the cap closed on this product. 4. Keep away from direct sunlight or heat. 5. Keep out of reach of children.

DESCRIPTION

How to use: Apply evenly to areas exposed to UV Rays such as your face and arms and allow it to absorb.